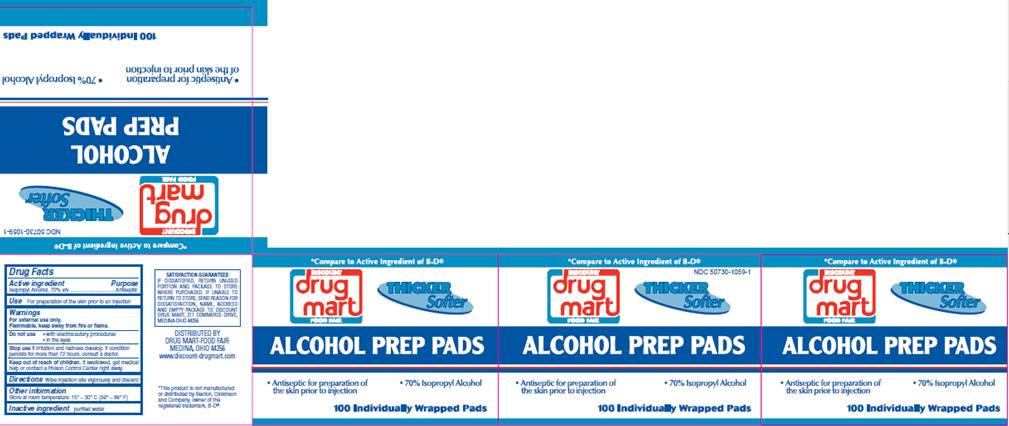 DRUG LABEL: Isopropyl alcohol Prep Pad
NDC: 50730-1059 | Form: SWAB
Manufacturer: H and P Industries, Inc. dba Triad Group
Category: otc | Type: HUMAN OTC DRUG LABEL
Date: 20091211

ACTIVE INGREDIENTS: Isopropyl alcohol .7 mL/1 1
INACTIVE INGREDIENTS: water

DRUG FACTS

ACTIVE INGREDIENT

Isopropyl Alcohol 70% v/v

PURPOSE

Antiseptic

USE

For preparation of the skin prior to an injection

WARNINGS

For external use only.
Flammable, keep away from fire or flame.

Do not use

- with electrocautery procedures
- in the eyes

Stop use

if irritation and redness develop. If condition persists for more than 72 hours, consult a doctor.

Keep out of reach of children

If swallowed, get medical help or contact a Poison Control Center right away.

DIRECTIONS

Wipe injection site vigorously and discard

OTHER INFORMATION

Store at room temperature 15° - 30° C (59° - 86° F)

INACTIVE INGREDIENT

purified water

PACKAGE INFORMATION

*Compare to Active Ingredient of B-D®
Discount Drug Mart Food Fair
Thicker
Softer
ALCOHOL PREP PADS

- Antiseptic for preparation of the skin prior to injection
- 70% Isopropyl Alcohol

100 Individually Wrapped Pads
SATISFACTION GUARANTEED
If dissatisfied, return unused portion and package to store where purchased. If unable to return to store, send reason for dissatisfaction, name, address, and empty package to Discount Drug Mart, 211 Commerce Drive, Medina, Ohio 44256
DISTRIBUTED BY
DRUG MART-FOOD FAIR
MEDINA, OHIO 44256
www.discount-drugmart.com
*This product is not manufactured or distributed by Becton Dickinson and company, owner of the registered trademark, B-D®.